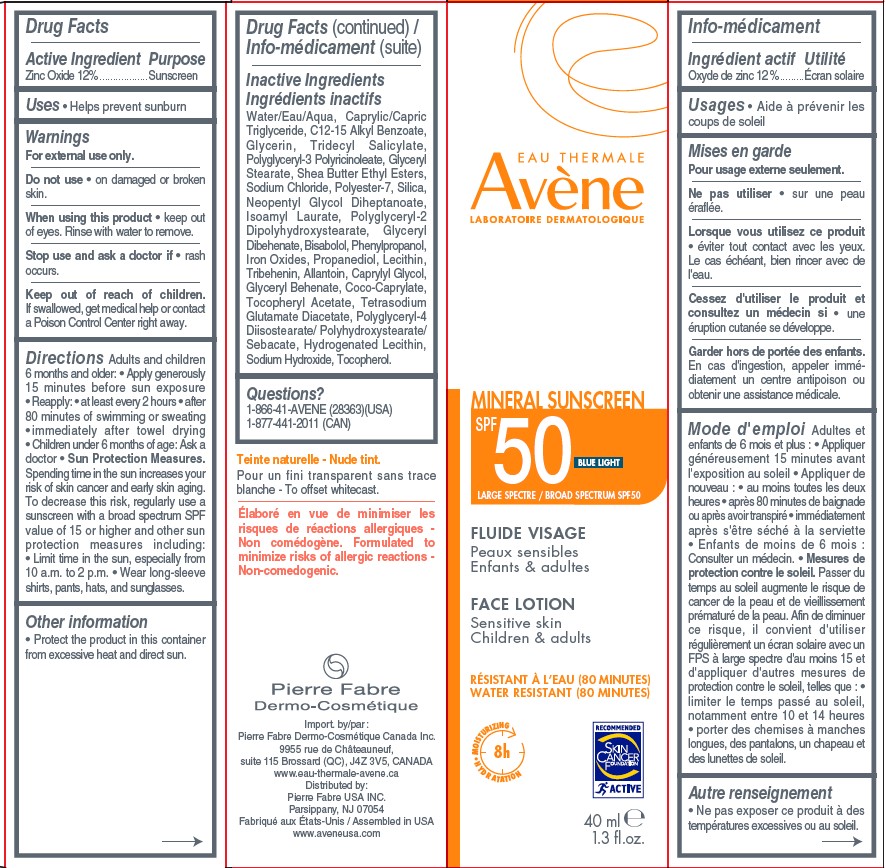 DRUG LABEL: Avene Face Sunscreen SPF 50
NDC: 64760-782 | Form: LOTION
Manufacturer: Pierre Fabre USA Inc.
Category: otc | Type: HUMAN OTC DRUG LABEL
Date: 20240308

ACTIVE INGREDIENTS: ZINC OXIDE 120 mg/1 mL
INACTIVE INGREDIENTS: MEDIUM-CHAIN TRIGLYCERIDES; ALKYL (C12-15) BENZOATE; GLYCERYL MONOSTEARATE; POLYGLYCERYL-2 DIPOLYHYDROXYSTEARATE; LEVOMENOL; PHENYLPROPANOL; ALLANTOIN; CAPRYLYL GLYCOL; GLYCERYL MONOBEHENATE; COCO-CAPRYLATE; TETRASODIUM GLUTAMATE DIACETATE; WATER; TRIDECYL SALICYLATE; HYDROGENATED SOYBEAN LECITHIN; TOCOPHEROL; SODIUM CHLORIDE; POLYESTER-7; ISOAMYL LAURATE; GLYCERYL DIBEHENATE; FERRIC OXIDE RED; PROPANEDIOL; LECITHIN, SOYBEAN; POLYGLYCERYL-4 DIISOSTEARATE/POLYHYDROXYSTEARATE/SEBACATE; SILICON DIOXIDE; TRIBEHENIN; SODIUM HYDROXIDE; GLYCERIN; POLYGLYCERYL-3 PENTARICINOLEATE; SHEA BUTTER ETHYL ESTERS; NEOPENTYL GLYCOL DIHEPTANOATE; ALPHA-TOCOPHEROL ACETATE

Avene Face Lotion SPF 50

Active Ingredient

Zinc Oxide 12%

Purpose

Sunscreen

Uses

• helps prevent sunburn.

• if used as directed with other sun protection measures (see Directions), decreases the risk of skin cancer and early skin aging caused by the sun.

Warnings

For external use only.

Do not use

• on broken skin.

When using this product

• keep out of eyes. Rinse with water to remove.

Stop use and ask a doctor if

• rash occurs.

Keep out of reach of children.

If swallowed, call a poison control center or get medical help right away.

Directions

Adults and children 6 months and older:

• Apply generously 15 minutes before sun exposure • Reapply: • at least every 2 hours • after 80 minutes of swimming or sweating • immediately after towel drying • Children under 6 months of age: Ask a doctor • Sun Protection Measures. Spending time in the sun increases your risk of skin cancer and early skin aging. To decrease this risk, regularly use a sunscreen with a broad spectrum SPF value of 15 or higher and other sun protection measures including: • Limit time in the sun, especially from 10 a.m. to 2 p.m. • Wear long-sleeve shirts, pants, hats, and sunglasses.

Inactive Ingredients

Water/Eau/Aqua, Caprylic/Capric Triglyceride, C12-15 Alkyl Benzoate, Glycerin, Tridecyl Salicylate, Polyglyceryl-3 Polyricinoleate, Glyceryl Stearate, Shea Butter Ethyl Esters, Sodium Chloride, Polyester-7, Silica, Neopentyl Glycol Diheptanoate, Isoamyl Laurate, Polyglyceryl-2 Dipolyhydroxystearate, Glyceryl Dibehenate, Bisabolol, Phenylpropanol, Iron Oxides, Propanediol, Lecithin, Tribehenin, Allantoin, Caprylyl Glycol,Glyceryl Behenate, Coco-Caprylate, Tocopheryl Acetate, Tetrasodium Glutamate Diacetate, Polyglyceryl-4
Diisostearate/ Polyhydroxystearate/Sebacate, Hydrogenated Lecithin, Sodium Hydroxide, Tocopherol.

Other information

• Protect the product in this container from excessive heat and direct sun.

Questions?

1-866-41-AVENE (28363)

1-877-441-2011 (CAN)